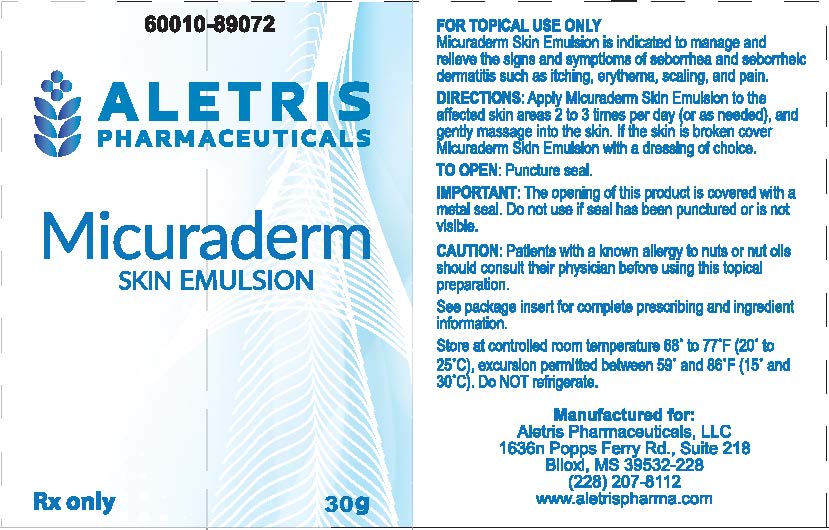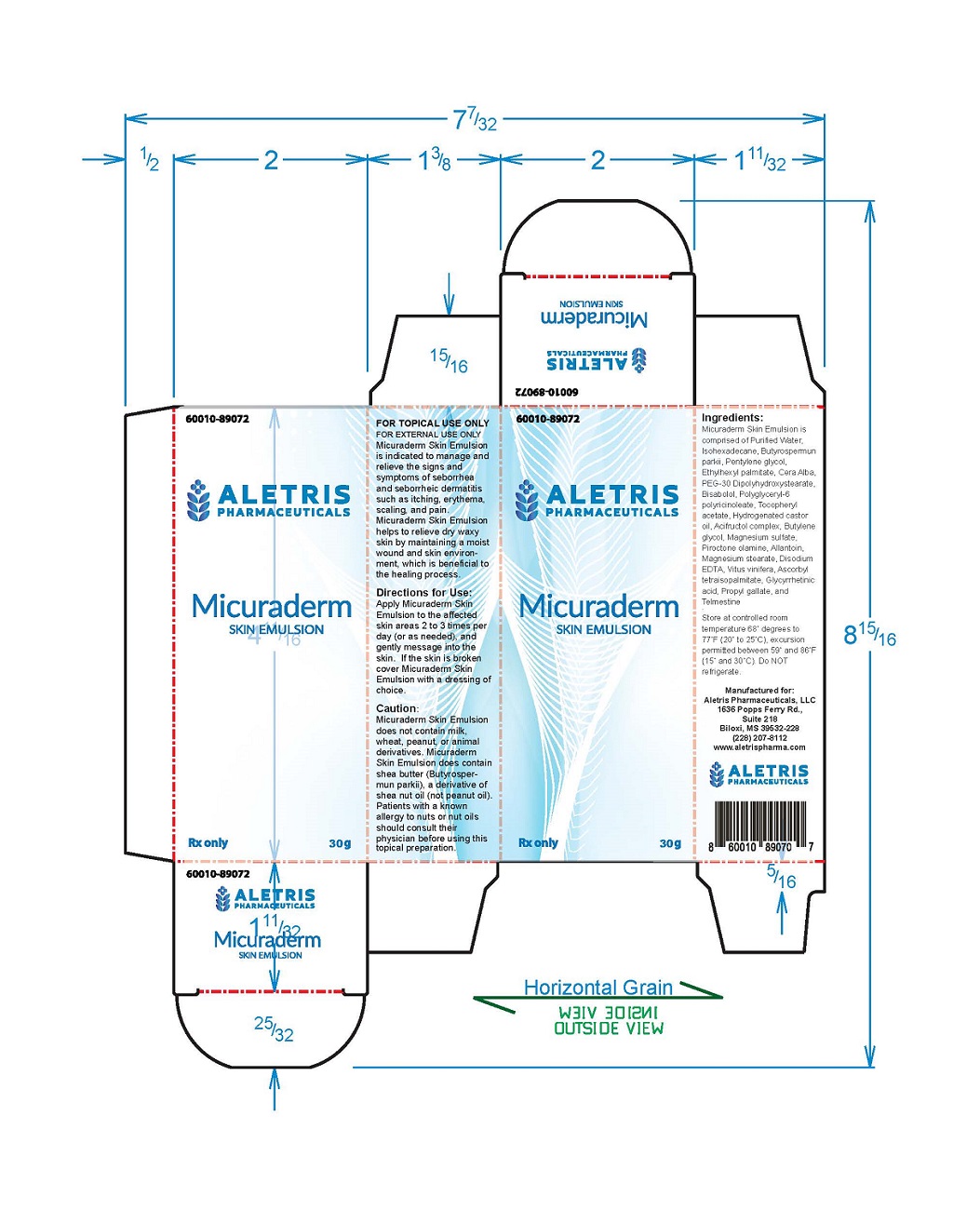 DRUG LABEL: Micuraderm
NDC: 86001089072
Manufacturer: Aletris Pharmaceuticals, LLC
Category: other | Type: PRESCRIPTION MEDICAL DEVICE LABEL
Date: 20231107

Micuraderm Skin Emulsion

For External Use Only For Topical Dematological Use Only

Rx Only 60010-89072

Product Description:

Micuraderm Skin Emulsion is an off dash white, steroid-free, fragrance-free, water-based, emulsion.

Indications for Use:

Under the supervision of a healthcare professional, Micuraderm Skin Emulsion is indicated to manage and relieve the signs and symptoms of seborrhea and seborrheic dermatitis such as itching, erythema, scaling, and pain. Micuraderm Skin Emulsion helps to relieve dry waxy skin by maintaining a moist wound and skin environment, which is beneficial to the healing process.

Directions for Use:

Apply Micuraderm Skin Emulsion to the affected skin areas 2 to 3 times per day (or as needed), and gently message into the skin. If the skin is broken cover Micuraderm Skin Emulsion with a dressing of choice.

Ingredients:

Micuraderm Skin Emulsion is comprised of Purified Water, lsohexadecane, Butyrospermun parkii, Pentylene glycol, Ethylhexyl palmitate, Cera Alba, PEG-30 Dipolyhydroxystearate, Bisabolol, Polyglyceryl-6 polyricinoleate, Tocopheryl acetate, Hydrogenated castor oil, Acifructol complex, Butylene glycol, Magnesium sulfate, Piroctone olamine, Allantoin, Magnesium stearate, Disodium EDTA, Vitus vinifera, Ascorbyl tetraisopalmitate, Glycyrrhetinic acid, Propyl gallate, and Telmestine.

Caution:

The use of Micuraderm Skin Emulsion is contraindicated in any patient with a known history of hypersensitivity to any of the ingredients. Micuraderm Skin Emulsion does not contain milk, wheat, peanut, or animal derivatives. Micuraderm Skin Emulsion does contain shea butter (Butyrospermun parkii), a derivative of shea nut oil (not peanut oil). Patients with a known allergy to nuts or nut oils should consult their physician before using this topical preparation.

How Supplied:

30g Tube

To Open: Puncture seal with pointed end of cap.

Important: The opening of this product is covered with a metal seal. Do no use If seal has been punctured or is not visible.

Store at controlled room temperature 68°degrees to 77°F (20° to 25°C), excursion permitted between 59° and 86°F (15° and 30°C). Do NOT refrigerate.

Manufactured for:

Aletris Pharmaceuticals, LLC

1636n Papps Ferry Rd., Suite 218

Biloxi, MS 39532-228

(228) 207-8112

www.aletrispharma.com